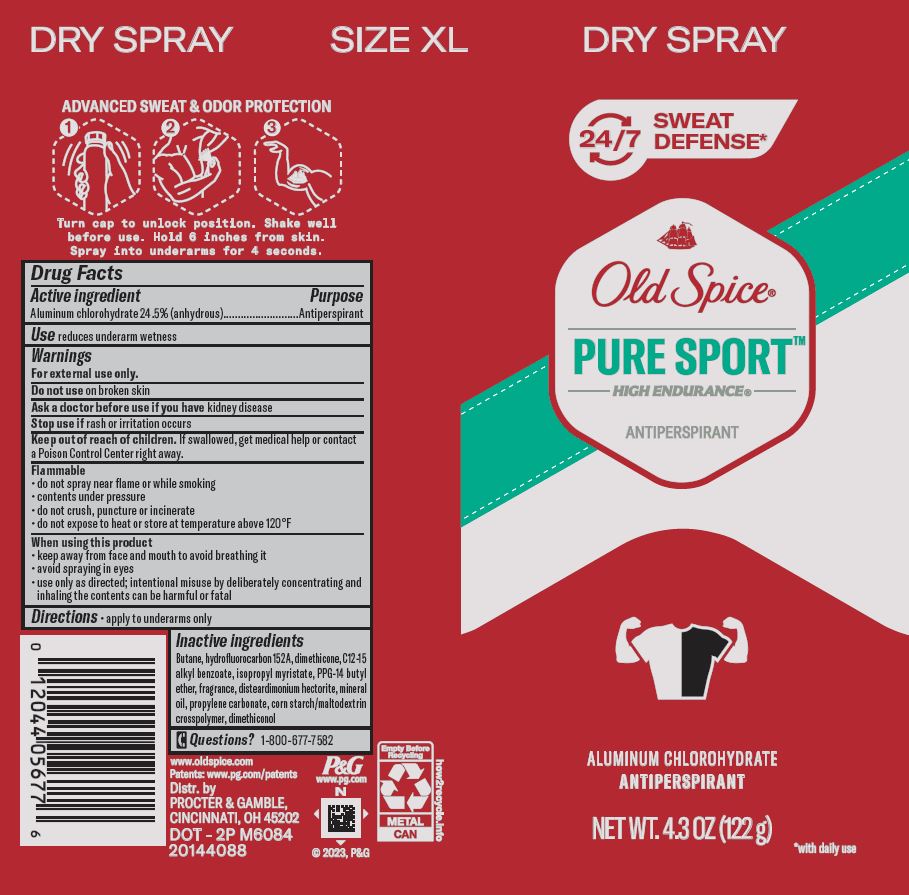 DRUG LABEL: Old Spice Pure Sport High Endurance Dry
NDC: 84126-039 | Form: AEROSOL, SPRAY
Manufacturer: The Procter & Gamble Manufacturing Company
Category: otc | Type: HUMAN OTC DRUG LABEL
Date: 20251231

ACTIVE INGREDIENTS: ALUMINUM CHLOROHYDRATE 24.5 g/100 g
INACTIVE INGREDIENTS: DIMETHICONE; MINERAL OIL; DIMETHICONOL (100000 CST); BUTANE; 1,1-DIFLUOROETHANE; C12-15 ALKYL BENZOATE; DISTEARDIMONIUM HECTORITE; PROPYLENE CARBONATE; ISOPROPYL MYRISTATE; PPG-14 BUTYL ETHER

Old Spice High Endurance Pure Sport Dry Spray

Drug Facts

Active ingredient

Aluminum chlorohydrate 24.5% (anhydrous)

Purpose

Antiperspirant

Use

- reduces underarm wetness

Warnings

For external use only.

Do not use on broken skin

Ask a doctor before use if you have kidney disease

Stop use if rash or irritation occurs

Keep out of reach of children. If swallowed, get medical help or contact a Poison Control Center right away.

When using this product

keep away from face and mouth to avoid breathing it

avoid spraying in eyes

use only as directed; intentional misuse by deliberately concentrating and inhaling the contents can be harmful or fatal

SAFE HANDLING WARNING

Flammable

do not spray near flame or while smoking

contents under pressure
do not crush, puncture or incinerate

do not expose to heat or store at temperature above 120ºF

Directions

- apply to underarms only

Inactive ingredients

Butane, hydrofluorocarbon 152A, dimethicone, C12-15 alkyl benzoate, isopropyl myristate, PPG-14 butyl ether, fragrance, disteardimonium hectorite,mineral oil, propylene carbonate, corn starch/maltodextrin crosspolymer, dimethiconol

Questions?

1-800-677-7582

Dist. by PROCTER & GAMBLE,
CINCINNATI, OH 45202.

PRINCIPAL DISPLAY PANEL - 122 g Can

SIZE XL DRY SPRAY

Old Spice ®

PURE SPORT

HIGH ENDURANCE

ANTIPERSPIRANT

ALUMINUM CHLOROHYDRATE

ANTIPERSPIRANT

NET WT. 4.3 OZ (122 g)